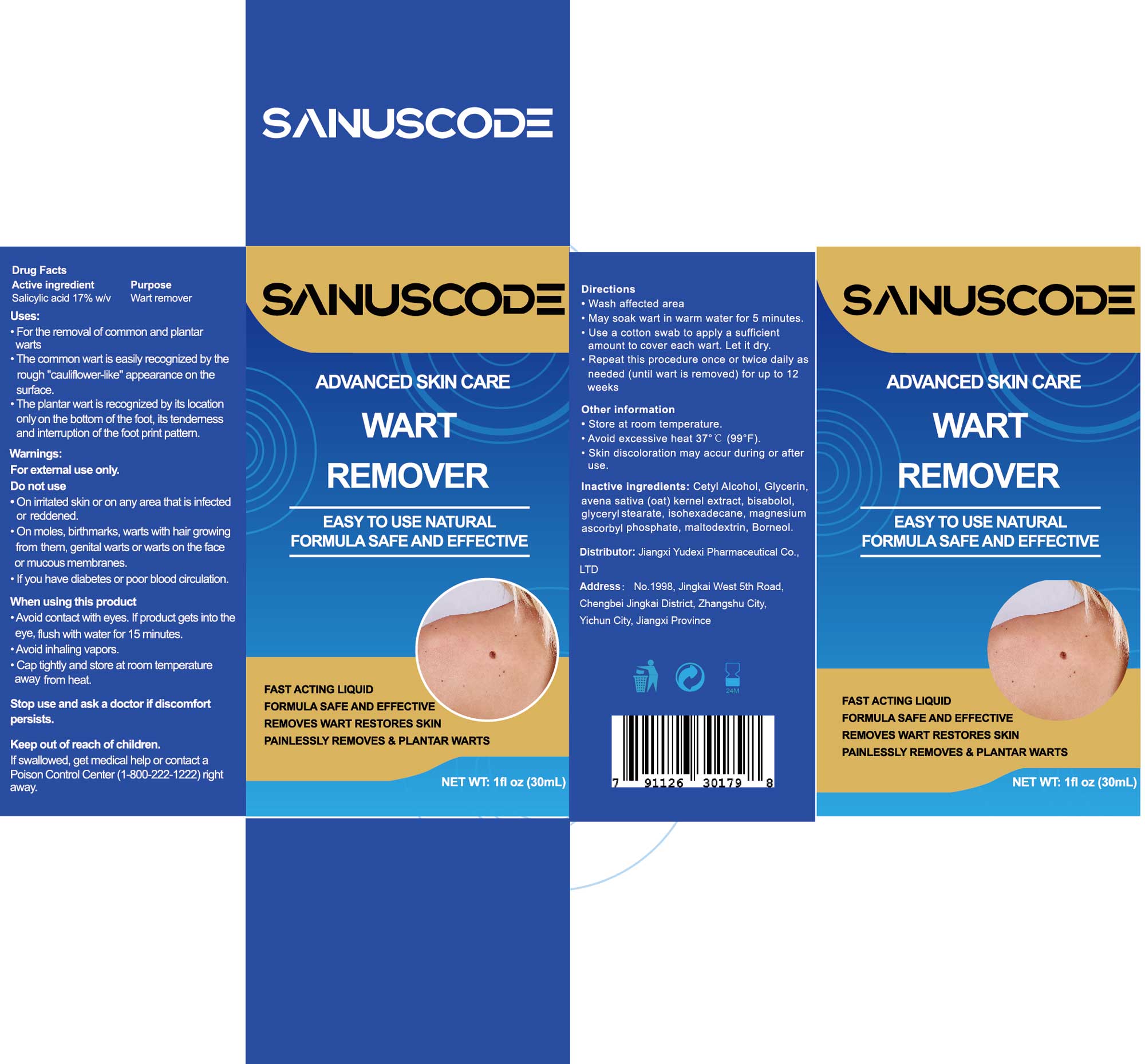 DRUG LABEL: SANUSCODE  WART REMOVER
NDC: 85248-050 | Form: LIQUID
Manufacturer: Jiangxi Yudexi Pharmaceutical Co., LTD
Category: otc | Type: HUMAN OTC DRUG LABEL
Date: 20260205

ACTIVE INGREDIENTS: SALICYLIC ACID 17 g/100 mL
INACTIVE INGREDIENTS: GLYCERIN; BISABOLOL; ISOHEXADECANE; MAGNESIUM ASCORBYL PHOSPHATE; MALTODEXTRIN; BORNEOL; AVENA SATIVA FLOWERING TOP; GLYCERYL STEARATE; CETYL ALCOHOL

85248-050

Active Ingredient

Salicylic acid 17% w/v

Purpose

Wart remover

Use

·For the removal of common and plantar warts ·The common wart is easily recognized by the rough “cauliflower-like”appearance on the surface. ·The plantar wart is recognized by its location only on the bottom of the foot, its tenderness and interruption of the footprint pattern

Warnings

For external use only.

Do not use

On irritated skin or on any area that is infected or reddened·On moles, birthmarks, warts with hair growing from them, genital warts or
warts on the face or mucous membranes.·If you have diabetes or poor blood circulation.

When Using

Avoid contact with eyes. If product gets into the eye, flush with water for 15 minutes.·Avoid inhaling vapors·Cap tightly and store at
room temperature away from heat

Stop Use

Stop use and ask a doctor if discomfort persists.

Ask Doctor

Stop use and ask a doctor if discomfort persists.

Keep Oot Of Reach Of Children

If swallowed, get medical help or contact a Poison Control Center (1-800-222-1222) right away.

Directions

·Wash affected area·May soak wart in warm water for 5 minutes ·Use a cotton swab to apply a sufficient amount to cover each wart·let it dry Repeat this procedure once or twice daily as needed (until wart is removed) for up to 12 weeks

Other information

·Store at room temperature·Avoid excessive heat 37°C (99°F)·Skin discoloration may accur during or after use

Inactive ingredients

Cetyl Alcohol,Glycerin, avena sativa (oat) kernel extract, bisabolol,glyceryl stearate, isohexadecane,magnesium ascorbyl phosphate,maltodextrin, Borneol.